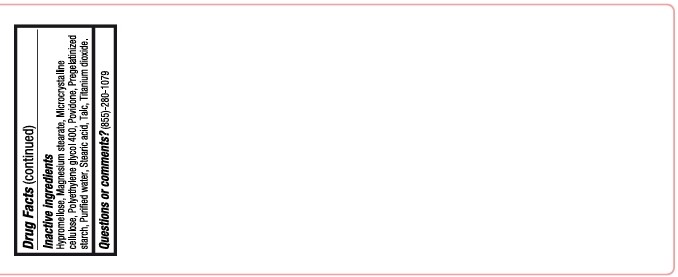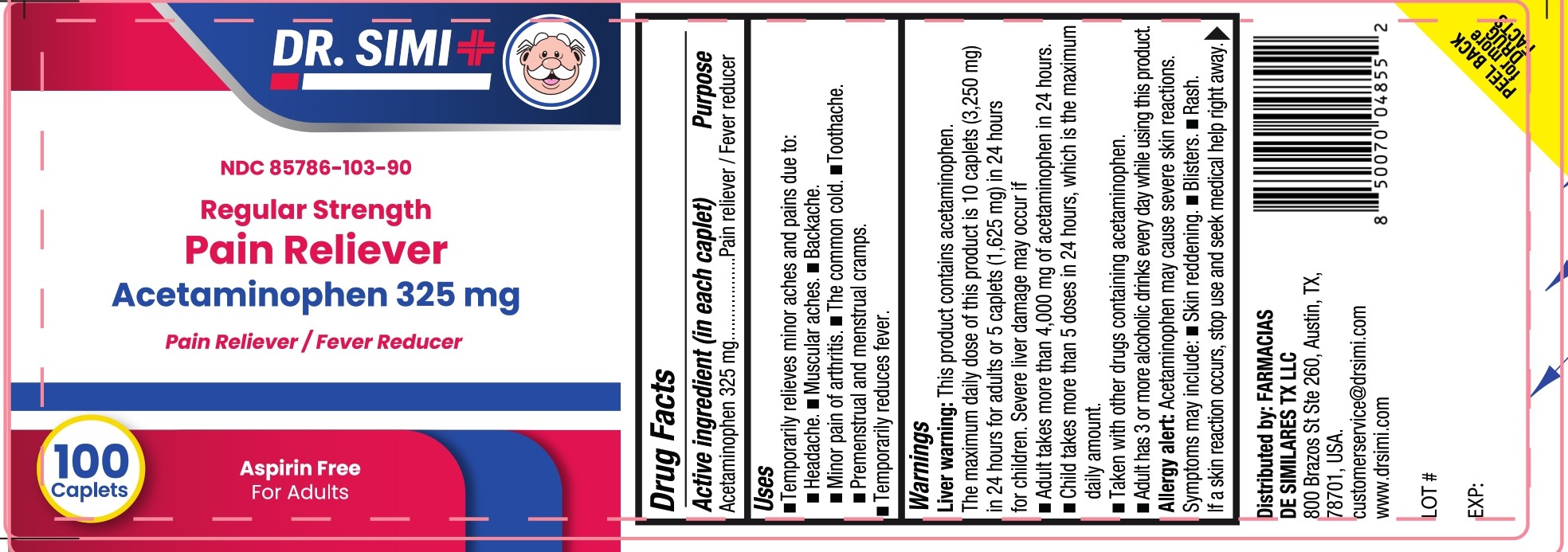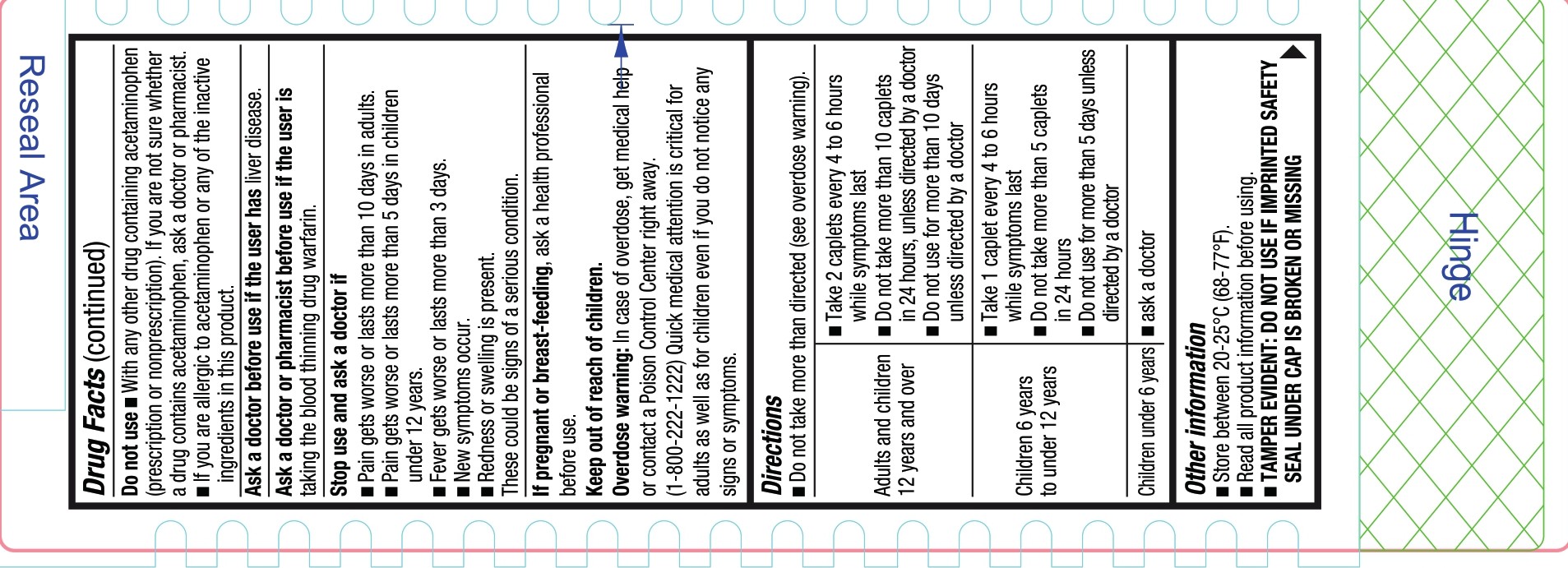 DRUG LABEL: Dr Simi Pain Relief
NDC: 85786-103 | Form: TABLET, COATED
Manufacturer: Farmacias De Similares TX LLC
Category: otc | Type: HUMAN OTC DRUG LABEL
Date: 20250813

ACTIVE INGREDIENTS: ACETAMINOPHEN 325 mg/1 1
INACTIVE INGREDIENTS: TITANIUM DIOXIDE; WATER; MAGNESIUM STEARATE; HYPROMELLOSES; POVIDONE K30; TALC; POLYETHYLENE GLYCOL 400; STARCH, CORN; MICROCRYSTALLINE CELLULOSE; STEARIC ACID

Pain reliever Acetaminophen 325 mg

Drug Facts

Active ingredient (in each caplet)

- Acetaminophen 325 mg

Purpose

Pain reliever / Fever reducer

Uses

- Temporarily relieves minor aches and pains due to:
- Headache.
- Muscular aches.
- Backache.
- Minor pain of arthritis.
- The common cold.
- Toothache.
- Premenstrual and menstrual cramps.
- Temporarily reduces fever.

Warnings

Liver warning: This product contains acetaminophen. The maximum daily dose of this product is 10 caplets (3,250 mg) in 24 hours for adults or 5 caplets (1,625 mg) in 24 hours for children. Severe liver damage may occur if:

- Adult takes more than 4,000 mg of acetaminophen in 24 hours.
- Child takes more than 5 doses in 24 hours, which is the maximum daily amount.
- Taken withother drugs containing acetaminophen.
- Adult has 3 or more alcoholic drinks every day while using this product.

Allergy alert: Acetaminophen may cause severe skin reactions.

Symptoms may include:

- Skin reddening.
- Blisters.
- Rash.

If a skin reaction occurs, stop use and seek medical help right away.

Do not use

- With any other drug containing acetaminophen (prescription or nonprescription). If you are not sure whether a drug contains acetaminophen, ask a doctor or pharmacist.
- if you are allergic to acetaminophen or any of the inactive ingredients in this product.

Ask a doctor before use if the user has

liver disease.

Ask a doctor or pharmacist before use if the user is

taking the blood thinning drug warfarin.

Stop use and ask doctor if

- Pain gets worse or lasts more than 10 days in adults.
- Pain gets worse or lasts more than 5 days in children under 12 years.
- Fever gets worse or lasts more than 3 days.
- New symptoms occur.
- Redness or swelling is present.

These could be signs of a serious condition.

If pregnant or breast-feeding

ask a health professional before use.

Keep Out of reach of Children

Overdose warning

Overdose warning: In case of overdose, get medical help or contact a Poison Control Center right away. (1-800-222-1222) Quick medical attention is critical for adults as well as for children even if you do not notice any signs or symptoms.

Directions

- Do not take more than directed (see overdose warning).

Directions

Adults and children 12 years and over | - Take 2 caplets every 4 to 6 hours while symptoms last. - Do not take more than 10 caplets in 24 hours, unless directed by a doctor. - Do not use for more than 10 days unless directed by a doctor.
Children 6 years to under 12 years | - Take 1 caplet every 4 to 6 hours while symptoms last. - Do not take more than 5 caplets in 24 hours. - Do not use for more than 5 days unless directed by a doctor.
Children under 6 years | Ask a doctor

Other information

- Store between 20-25°C (68-77°F).
- Read all product information before using.

TAMPER EVIDENT: DO NOT USE IF IMPRINTED SAFETY SEAL UNDER CAP IS BROKEN OR MISSING

Inactive ingredients

Hypromellose, Magnesium stearate, Microcrystalline Cellulose , Polyethylene glycol 400, Povidone, Pregelatinized Starch, Purified water, Stearic acid , Talc, Titanium Dioxide.

Questions or comments?

(855)-280-1079

Distributed by: FARMACIAS DE SIMILARES TX LLC

800 Brazos St Ste 260, Austin, TX, 78701, USA.

customerservice@drsimi.com

www.drsimi.com

LOT#

EXP:

PEEL BACK for more DRUG FACTS

Principal display panel

DR SIMI

NDC 85786-103-90

Regular Strength

Pain Reliever

Acetaminophen 325 mg

Pain Reliever/ Fever Reducer

100 Caplets

Aspirin Free

For Adults